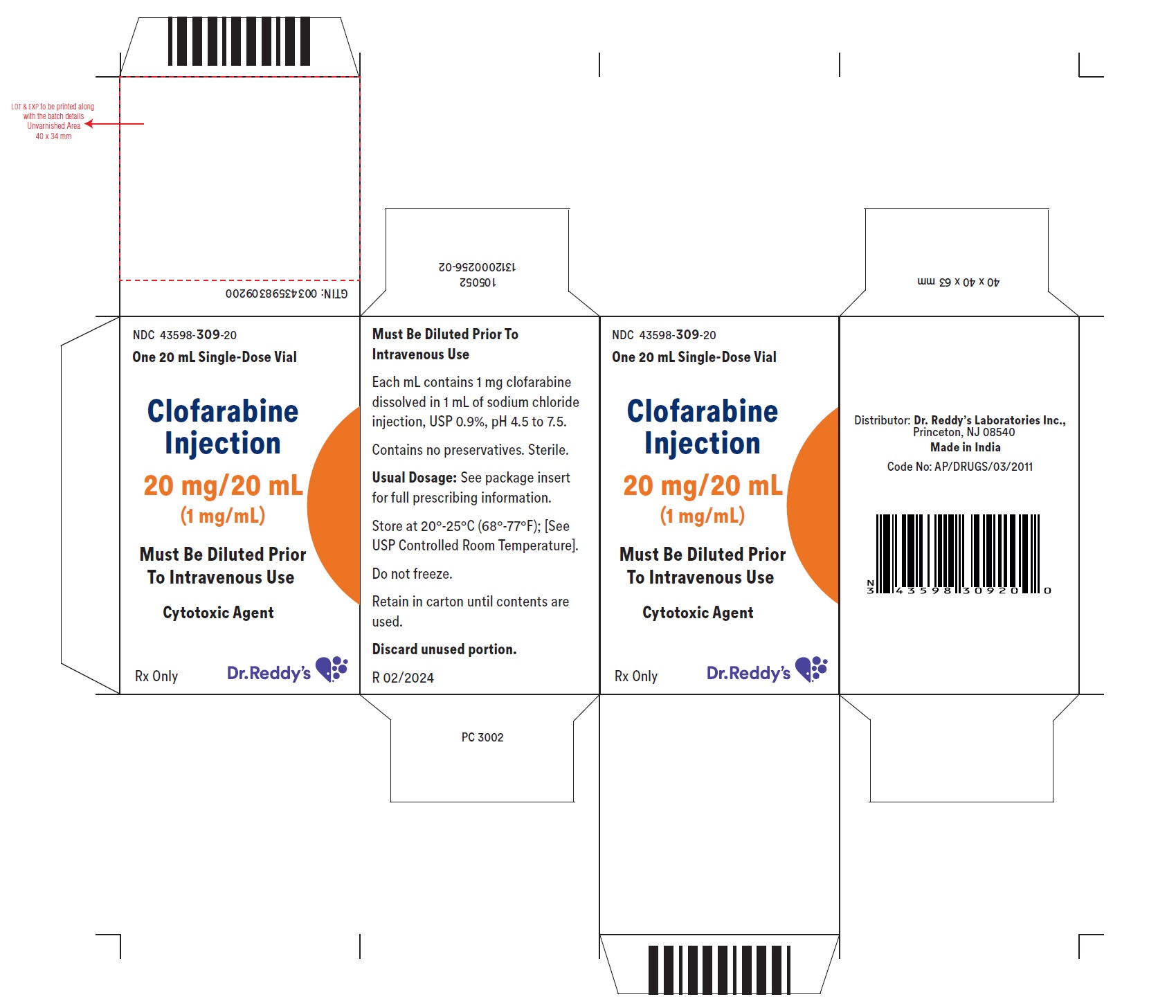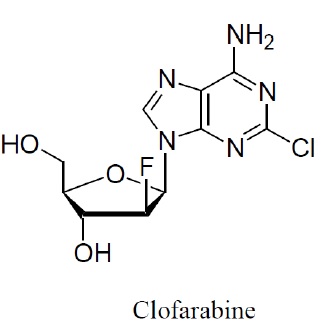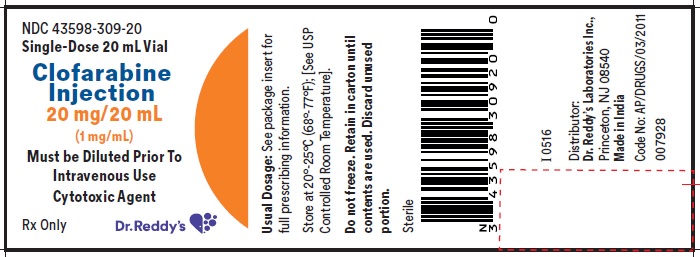 DRUG LABEL: Clofarabine
NDC: 43598-309 | Form: INJECTION
Manufacturer: Dr.Reddy's Laboratories Inc
Category: prescription | Type: HUMAN PRESCRIPTION DRUG LABEL
Date: 20240227

ACTIVE INGREDIENTS: CLOFARABINE 1 mg/1 mL
INACTIVE INGREDIENTS: SODIUM CHLORIDE

HIGHLIGHTS OF PRESCRIBING INFORMATION

These highlights do not include all the information needed to use CLOFARABINE INJECTION safely and effectively. See full prescribing information for CLOFARABINE INJECTION.
CLOFARABINE injection, for intravenous use
Initial U.S. Approval: 2004

RECENT MAJOR CHANGES

Indications and Usage (1) 7/2022

1 INDICATIONS AND USAGE

Clofarabine injection is a nucleoside metabolic inhibitor indicated for the treatment of pediatric patients 1 to 21 years old with relapsed or refractory acute lymphoblastic leukemia after at least two prior regimens. (1)

2 DOSAGE AND ADMINISTRATION

- Administer the recommended pediatric dose of 52 mg/m^2as an intravenous infusion over 2 hours daily for 5 consecutive days of a 28-day cycle. Repeat cycles every 2 to 6 weeks. (2.1)
- Provide supportive care, such as intravenous infusion fluids, antihyperuricemic treatment and alkalinization of urine throughout the 5 days of clofarabine injection administration to reduce the risk of tumor lysis and other adverse reactions. (2.1)
- Discontinue clofarabine injection if hypotension develops during the 5 days of administration. (2.1)
- Reduce the dose in patients with renal impairment. (2.2)
- Use dose modification for toxicity. (2.4)

3 DOSAGE FORMS AND STRENGTHS

• Injection: 20 mg/20 mL (1 mg/mL) single-dose vial. (3)

4 CONTRAINDICATIONS

• None. (4)

5 WARNINGS AND PRECAUTIONS

- Myelosuppression: May be severe and prolonged. Monitor complete blood counts and platelet counts during clofarabine injection therapy. (5.1)
- Hemorrhage: Serious and fatal cerebral, gastrointestinal and pulmonary hemorrhage. Monitor platelets and coagulation parameters and treat accordingly. (5.2)
- Infections: Severe and fatal sepsis as a result of bone marrow suppression. Monitor for signs and symptoms of infection; discontinue clofarabine injection and treat promptly. (5.3)
- Tumor Lysis syndrome: Anticipate, monitor for signs and symptoms and treat promptly. (5.4)
- Systemic Inflammatory Response Syndrome (SIRS) or Capillary Leak Syndrome: Monitor for and discontinue clofarabine injection immediately if suspected. (5.5)
- Venous Occlusive Disease of the Liver: Monitor for and discontinue clofarabine injection if suspected. (5.6)
- Hepatotoxicity: Severe and fatal hepatotoxicity. Monitor liver function, for signs and symptoms of hepatitis and hepatic failure. Discontinue clofarabine injection immediately for Grade 3 or greater liver enzyme and/or bilirubin elevations. (5.7)
- Renal Toxicity: Increased creatinine and acute renal failure; monitor renal function and interrupt or discontinue clofarabine injection. (5.8)
- Enterocolitis: Serious and fatal enterocolitis, occurring more frequently within 30 days of treatment and with combination chemotherapy. Monitor patients for signs and symptoms of enterocolitis and treat promptly (5.9)
- Skin Reactions: Stevens-Johnson syndrome (SJS) and toxic epidermal necrolysis (TEN), including fatal cases. Discontinue for exfoliative or bullous rash, or if SJS or TEN is suspected. (5.10)
- Embryo-Fetal Toxicity: Can cause fetal harm. Advise females of reproductive potential and males with female partners of reproductive potential of the potential risk to a fetus and to use effective contraception. (5.11)

6 ADVERSE REACTIONS

Most common adverse reactions (≥25%): vomiting, nausea, diarrhea, febrile neutropenia, pruritus, headache, bacteremia, pyrexia, rash, tachycardia, abdominal pain, chills, fatigue, anorexia, pain in extremity, hypotension, epistaxis, and petechiae. (6)

To report SUSPECTED ADVERSE REACTIONS, contact Dr. REDDY’S LABORATORIES Inc., at 1-888-375-3784 or FDA at 1-800-FDA-1088 or www.fda.gov/medwatch.

8 USE IN SPECIFIC POPULATIONS

• Lactation: Advise not to breastfeed. (8.2)

FULL PRESCRIBING INFORMATION

1 INDICATIONS AND USAGE

Clofarabine injection is indicated for the treatment of pediatric patients 1 to 21 years old with relapsed or refractory acute lymphoblastic leukemia after at least two prior regimens.

2 DOSAGE AND ADMINISTRATION

2.1 Recommended Dosage

Administer the recommended pediatric dose of 52 mg/m^2 as an intravenous infusion over 2 hours daily for 5 consecutive days.

• Repeat treatment cycles following recovery or return to baseline organ function, approximately every 2 to 6 weeks. Base dosage on the patient’s body surface area (BSA), calculatedusing the actual height and weight before the start of each cycle. To prevent drug incompatibilities, do not administer other medications through the same intravenous line. Administer subsequent cycles no sooner than 14 days from the starting day of the previous cycle and provided the patient’s ANC is ≥0.75 × 10^9/L.

• Provide supportive care, such as intravenous fluids, antihyperuricemic treatment, and alkalinize urine throughout the 5 days of clofarabine injection administration to reduce the effects of tumor lysis and other adverse reactions.

• Discontinue clofarabine injection if hypotension develops during the 5 days of administration.

• Monitor renal and hepatic function during the 5 days of clofarabine injection administration [see Warnings and Precautions (5.7, 5.8)].

• Monitor patients taking medications known to affect blood pressure. Monitor cardiac function during administration of clofarabine injection.

2.2 Recommended Dosage Reduction for Renal Impairment

• Reduce the dose by 50% in patients with creatinine clearance (CrCL) between 30 and 60 mL/min. There is insufficient information to make a dosage recommendation in patients with CrCL less than 30 mL/min [see Use in Specific Populations (8.6)].

2.3 Potential Concomitant Medications and Medications to Avoid

• Consider prophylactic antiemetic medications as clofarabine injection is moderately emetogenic.

• Consider the use of prophylactic steroids to mitigate Systemic Inflammatory Response Syndrome (SIRS) or capillary leak syndrome (e.g., hypotension, tachycardia, tachypnea, and pulmonary edema).

• Minimize exposure to drugs with known renal toxicity during the 5 days of clofarabine injection administration since the risk of renal toxicity may be increased.

• Avoid concomitant use of medications known to induce hepatic toxicity.

2.4 Dose Modifications and Reinitiation of Therapy after Adverse Reactions

Hematologic Toxicity

• If a patient experiences a Grade 4 neutropenia (ANC <0.5 x 10^9/L) lasting ≥4 weeks, reduce dose by 25% for the next cycle.

Non-hematologic Toxicity

• Withhold clofarabine injection if a patient develops a clinically significant infection, until the infection is controlled, then restart at the full dose.

• Withhold clofarabine injection for a Grade 3 non-infectious non-hematologic toxicity (excluding transient elevations in serum transaminases and/or serum bilirubin and/or nausea/vomiting controlled by antiemetic therapy). Re-institute clofarabine injection administration at a 25% dose reduction when resolution or return to baseline.

• Discontinue clofarabine injection administration for a Grade 4 non-infectious nonhematologic toxicity.

• Discontinue clofarabine injection administration if a patient shows early signs or symptoms of SIRS or capillary leak syndrome (e.g., hypotension, tachycardia, tachypnea, and pulmonary edema) occur and provide appropriate supportive measures.

• Discontinue clofarabine injection administration if Grade 3 or higher increases in creatinine or bilirubin are noted. Re-institute clofarabine injection with a 25% dose reduction, when the patient is stable and organ function has returned to baseline. If hyperuricemia is anticipated (tumor lysis), initiate measures to control uric acid.

2.5 Reconstitution/Preparation

Filter clofarabine injection through a sterile 0.2 micron syringe filter and then dilute with 5% Dextrose Injection, USP, or 0.9% Sodium Chloride Injection, USP, prior to intravenous infusion to a final concentration between 0.15 mg/mL and 0.4 mg/mL. Use within 24 hours of preparation. Parenteral drug products should be visually inspected for particulate matter and discoloration prior to administration, whenever solution and container permit. Store diluted clofarabine injection at room temperature (20º-25ºC).

Discard unused portion in vial.

3 DOSAGE FORMS AND STRENGTHS

Injection: 20 mg/20 mL (1 mg/mL) clear solution in single-dose vial

4 CONTRAINDICATIONS

None.

5 WARNINGS AND PRECAUTIONS

5.1 Myelosuppression

Clofarabine injection causes myelosuppression which may be severe and prolonged. Febrile neutropenia occurred in 55% and non-febrile neutropenia in an additional 10% of pediatric patients in clinical trials. At initiation of treatment, most patients in the clinical studies had hematological impairment as a manifestation of leukemia. Myelosuppression is usually reversible with interruption of clofarabine injection treatment and appears to be dose-dependent. Monitor complete blood counts [see Dosage and Administration (2.4)].

5.2 Hemorrhage

Serious and fatal hemorrhage, including cerebral, gastrointestinal and pulmonary hemorrhage, has occurred. The majority of the cases were associated with thrombocytopenia. Monitor platelets and coagulation parameters and treat accordingly [see Adverse Reactions (6.2)].

5.3 Infections

Clofarabine injection increases the risk of infection, including severe and fatal sepsis, and opportunistic infections. At baseline, 48% of the pediatric patients had one or more concurrent infections. A total of 83% of patients experienced at least one infection after clofarabine injection treatment, including fungal, viral and bacterial infections. Monitor patients for signs and symptoms of infection, discontinue clofarabine injection, and treat promptly.

5.4 Tumor Lysis Syndrome

Administration of clofarabine injection may result in tumor lysis syndrome associated with the break down metabolic products from peripheral leukemia cell death. Monitor patients undergoing treatment for signs and symptoms of tumor lysis syndrome and initiate preventive measures including adequate intravenous fluids and measures to control uric acid.

5.5 Systemic Inflammatory Response Syndrome (SIRS) and Capillary Leak Syndrome

Clofarabine injection may cause a cytokine release syndrome (e.g., tachypnea, tachycardia, hypotension, pulmonary edema) that may progress to the systemic inflammatory response syndrome (SIRS) with capillary leak syndrome and organ impairment which may be fatal. Monitor patients frequently for these conditions. In clinical trials, SIRS was reported in two patients (2%); capillary leak syndrome was reported in four patients (4%). Symptoms included rapid onset of respiratory distress, hypotension, pleural and pericardial effusion, and multiorgan failure. Close monitoring for this syndrome and early intervention may reduce the risk. Immediately discontinue clofarabine injection and provide appropriate supportive measures. The use of prophylactic steroids (e.g., 100 mg/m^2 hydrocortisone on Days 1 through 3) may be of benefit in preventing signs or symptoms of SIRS or capillary leak syndrome. Consider use of diuretics and/or albumin. After the patient is stabilized and organ function has returned to baseline, retreatment with clofarabine injection can be considered with a 25% dose reduction.

5.6 Venous Occlusive Disease of the Liver

Patients who have previously received a hematopoietic stem cell transplant (HSCT) are at higher risk for veno-occlusive disease (VOD) of the liver following treatment with clofarabine (40 mg/m^2) when used in combination with etoposide (100 mg/m^2) and cyclophosphamide (440 mg/m^2). Severe hepatotoxic events have been reported in a combination study of clofarabine in pediatric patients with relapsed or refractory acute leukemia. Two cases (2%) of VOD in the monotherapy studies were considered related to study drug. Monitor for and discontinue clofarabine injection if VOD is suspected.

5.7 Hepatotoxicity

Severe and fatal hepatotoxicity, including hepatitis and hepatic failure, has occurred with the use of clofarabine injection. In clinical studies, Grade 3 to 4 liver enzyme elevations were observed in pediatric patients during treatment with clofarabine at the following rates: elevated aspartate aminotransferase (AST) occurred in 36% of patients; elevated alanine aminotransferase (ALT) occurred in 44% of patients. AST and ALT elevations typically occurred within 10 days of clofarabine administration and returned to Grade 2 or less within 15 days. Grade 3 or 4 elevated bilirubin occurred in 13% of patients, with 2 events reported as Grade 4 hyperbilirubinemia (2%), one of which resulted in treatment discontinuation and one patient had multiorgan failure and died. Eight patients (7%) had Grade 3 or 4 elevations in serum bilirubin at the last time point measured; these patients died due to sepsis and/or multiorgan failure. Monitor hepatic function, and for signs and symptoms of hepatitis and hepatic failure. Discontinue clofarabine injection immediately for Grade 3 or greater liver enzyme and/or bilirubin elevations [see Dosage and Administration (2.4)].

5.8 Renal Toxicity

Clofarabine injection may cause acute renal failure. In clofarabine injection treated patients in clinical studies, Grade 3 or 4 elevated creatinine occurred in 8% of patients and acute renal failure was reported as Grade 3 in three patients (3%) and Grade 4 in two patients (2%). Patients with infection, sepsis, or tumor lysis syndrome may be at increased risk of renal toxicity when treated with clofarabine injection. Hematuria occurred in 13% of clofarabine injection treated patients overall. Monitor patients for renal toxicity and interrupt or discontinue clofarabine injection as necessary [see Dosage and Administration (2.4)].

5.9 Enterocolitis

Fatal and serious cases of enterocolitis, including neutropenic colitis, cecitis, and C. difficile colitis, have occurred during treatment with clofarabine. This has occurred more frequently within 30 days of treatment, and in the setting of combination chemotherapy. Enterocolitis may lead to necrosis, perforation, hemorrhage or sepsis complications. Monitor patients for signs and symptoms of enterocolitis and treat promptly.

5.10 Skin Reactions

Serious and fatal cases of Stevens-Johnson syndrome (SJS) and toxic epidermal necrolysis (TEN) have been reported. Discontinue clofarabine for exfoliative or bullous rash, or if SJS or TEN is suspected [see Adverse Reactions (6.2)].

5.11 Embryo-Fetal Toxicity

Based on findings from animal reproductive studies and the drug’s mechanism of action, clofarabine can cause fetal harm when administered to a pregnant woman. Intravenous doses of clofarabine in rats and rabbits administered during organogenesis at doses that were below the maximum recommended human dose of 52 mg/m^2 based on body surface area (mg/m^2) caused an increase in resorptions, malformations, and variations. Advise females of reproductive potential of the potential risk to a fetus and to use an effective method of contraception during treatment with clofarabine and for 6 months after the last dose. Advise males with female partners of reproductive potential to use effective contraception during treatment with clofarabine and for 3 months after the last dose [see Use in Specific Populations (8.1)].

6 ADVERSE REACTIONS

The following clinically significant adverse reactions are discussed in greater detail in other sections of the label:

• Myelosuppression [see Warnings and Precautions (5.1)]

• Hemorrhage [see Warnings and Precautions (5.2)]

• Serious Infections [see Warnings and Precautions (5.3)]

• Hyperuricemia (tumor lysis syndrome) [see Warnings and Precautions (5.4)]

• Systemic Inflammatory Response Syndrome (SIRS) and Capillary Leak Syndrome [see Warnings and Precautions (5.5)]

• Venous Occlusive Disease of the Liver [see Warnings and Precautions (5.6)]

• Hepatotoxicity [see Warnings and Precautions (5.7)]

• Renal Toxicity [see Warnings and Precautions (5.8)]

• Enterocolitis [see Warnings and Precautions (5.9)]

• Skin Reactions [see Warnings and Precautions (5.10)]

6.1 Clinical Trials Experience

Because clinical trials are conducted under widely varying conditions, adverse reaction rates observed in the clinical trials of a drug cannot be directly compared to rates in the clinical trials of another drug and may not reflect the rates observed in practice.

The data described below reflect exposure to clofarabine in 115 pediatric patients with relapsed or refractory Acute Lymphoblastic Leukemia (ALL) (70 patients) or Acute Myelogenous Leukemia (AML) (45 patients).

In total, 115 pediatric patients treated in clinical trials received the recommended dose of clofarabine 52 mg/m^2 daily x 5. The median number of cycles was 2. The median cumulative amount of clofarabine received by pediatric patients during all cycles was 540 mg.

Most common adverse reactions (≥25%): vomiting, nausea, diarrhea, febrile neutropenia, pruritus, headache, bacteremia, pyrexia, rash, tachycardia, abdominal pain, chills, fatigue, anorexia, pain in extremity, hypotension, epistaxis, and petechiae.

Table 1 lists adverse reactions by System Organ Class, including severe or life threatening (NCI CTCAE Grade 3 or Grade 4), reported in ≥5% of the 115 patients in the 52 mg/m^2/day dose group (pooled analysis of pediatric patients with ALL and AML). More detailed information and follow-up of certain events is given below.

Table 1: Most Commonly Reported (≥5% Overall) Adverse Reactions by System Organ Class (N=115 pooled analysis)

System Organ Class¹ | Adverse Reaction (MedDRA Preferred Term)¹ | ALL/AML (All Grades, N=115) |  | Worst Grade (NCICommon Terminology Criteria)¹
 |  |  |  | 3 |  | 4 |  | 5
 |  | N | % | N | % | N | % | N | %
Blood and Lymphatic System Disorders | Febrile neutropenia | 63 | 55 | 59 | 51 | 3 | 3 | . | .
 | Neutropenia | 11 | 10 | 3 | 3 | 8 | 7 | . | .
Cardiac Disorders | Pericardial effusion | 9 | 8 | . | . | 1 | 1 | . | .
 | Tachycardia | 40 | 35 | 6 | 5 | . | . | . | .
Gastrointestinal Disorders | Abdominal pain | 40 | 35 | 8 | 7 | . | . | . | .
 | Abdominal pain upper | 9 | 8 | 1 | 1 | . | . | . | .
 | Diarrhea | 64 | 56 | 14 | 12 | . | . | . | .
 | Gingival or mouth bleeding | 20 | 17 | 8 | 7 | 1 | 1 | . | .
 | Nausea | 84 | 73 | 16 | 14 | 1 | 1 | . | .
 | Oral mucosal petechiae | 6 | 5 | 4 | 4 | . | . | . | .
 | Proctalgia | 9 | 8 | 2 | 2 | . | . | . | .
 | Stomatitis | 8 | 7 | 1 | 1 | . | . | . | .
 | Vomiting | 90 | 78 | 9 | 8 | 1 | 1 | . | .
GeneralDisorders and Administration Site Conditions | Asthenia | 12 | 10 | 1 | 1 | 1 | 1 | . | .
 | Chills | 39 | 34 | 3 | 3 | . | . | . | .
 | Fatigue | 39 | 34 | 3 | 3 | 2 | 2 | . | .
 | Irritability | 11 | 10 | 1 | 1 | . | . | . | .
 | Mucosal inflammation | 18 | 16 | 2 | 2 | . | . | . | .
 | Edema | 14 | 12 | 2 | 2 | . | . | . | .
 | Pain | 17 | 15 | 7 | 6 | 1 | 1 | . | .
 | Pyrexia | 45 | 39 | 16 | 14 | . | . | . | .
HepatobiliaryDisorder | Jaundice | 9 | 8 | 2 | 2 | . | . | . | .
Infections and Infestations | Bacteremia | 10 | 9 | 10 | 9 | . | . | . | .
 | Candidiasis | 8 | 7 | 1 | 1 | . | . | . | .
 | Catheter related infection | 14 | 12 | 13 | 11 | . | . | . | .
 | Cellulitis | 9 | 8 | 7 | 6 | . | . | . | .
 | Clostridium colitis | 8 | 7 | 6 | 5 | . | . | . | .
 | Herpes simplex | 11 | 10 | 6 | 5 | . | . | . | .
 | Herpes zoster | 8 | 7 | 6 | 5 | . | . | . | .
 | Oral candidiasis | 13 | 11 | 2 | 2 | . | . | . | .
 | Pneumonia | 11 | 10 | 6 | 5 | 1 | 1 | 1 | 1
 | Sepsis, including septic shock | 19 | 17 | 6 | 5 | 4 | 4 | 9 | 8
 | Staphylococcal bacteremia | 7 | 6 | 5 | 4 | 1 | 1 | . | .
 | Staphylococcal sepsis | 6 | 5 | 5 | 4 | 1 | 1 | . | .
 | Upper respiratory tract infection | 6 | 5 | 1 | 1 | . | . | . | .
Metabolismand Nutrition Disorders | Anorexia | 34 | 30 | 6 | 5 | 8 | 7 | . | .
Musculoskeletal andConnective TissueDisorders | Arthralgia | 10 | 9 | 3 | 3 | . | . | . | .
 | Back pain | 12 | 10 | 3 | 3 | . | . | . | .
 | Bone pain | 11 | 10 | 3 | 3 | . | . | . | .
 | Myalgia | 16 | 14 | . | . | . | . | . | .
 | Pain in extremity | 34 | 30 | 6 | 5 | . | . | . | .
Neoplasms Benign, Malignant and Unspecified (incl. cysts and polyps) | Tumor lysis syndrome | 7 | 6 | 7 | 6 | . | . | . | .
Nervous System Disorders | Headache | 49 | 43 | 6 | 5 | . | . | . | .
 | Lethargy | 12 | 10 | 1 | 1 | . | . | . | .
 | Somnolence | 11 | 10 | 1 | 1 | . | . | . | .
Psychiatric Disorders | Agitation | 6 | 5 | 1 | 1 | . | . | . | .
 | Anxiety | 24 | 21 | 2 | 2 | . | . | . | .
Renal and UrinaryDisorders | Hematuria | 15 | 13 | 2 | 2 | . | . | . | .
Respiratory, Thoracic and Mediastinal Disorders | Dyspnea | 15 | 13 | 6 | 5 | 2 | 2 | . | .
 | Epistaxis | 31 | 27 | 15 | 13 | . | . | . | .
 | Pleural effusion | 14 | 12 | 4 | 4 | 2 | 2 | . | .
 | Respiratory distress | 12 | 10 | 5 | 4 | 4 | 4 | 1 | 1
 | Tachypnea | 10 | 9 | 4 | 4 | 1 | 1 | . | .
Skin and SubcutaneousTissue Disorders | Erythema | 13 | 11 | . | . | . | . | . | .
 | Palmar-plantarerythrodysesthesiasyndrome | 18 | 16 | 8 | 7 | . | . | . | .
 | Palmar-plantarerythrodysesthesiasyndrome | 18 | 16 | 8 | 7 | . | . | . | .
 | Palmar-plantarerythrodysesthesiasyndrome | 18 | 16 | 8 | 7 | . | . | . | .
 | Palmar-plantarerythrodysesthesiasyndrome | 18 | 16 | 8 | 7 | . | . | . | .
 | Petechiae | 30 | 26 | 7 | 6 | . | . | . | .
 | Pruritus | 49 | 43 | 1 | 1 | . | . | . | .
 | Rash | 44 | 38 | 8 | 7 | . | . | . | .
 | Rash pruritic | 9 | 8 | . | . | . | . | . | .
Vascular Disorders | Flushing | 22 | 19 | . | . | . | . | . | .
 | Hypertension | 15 | 13 | 6 | 5 | . | . | . | .
 | Hypotension | 33 | 29 | 13 | 11 | 9 | 8 | . | .

¹ Patients with more than one adverse reaction (MedDRA preferred term) within a SOC are counted only once in the SOC totals. Patients with more than one occurrence of the same adverse reaction (MedDRA preferred term) are counted only once within that reaction and at the highest severity grade.

The following adverse reactions were reported in <5% of the 115 pediatric patients with ALL or AML:

Gastrointestinal Disorders: cecitis, pancreatitis

Hepatobiliary Disorders: hyperbilirubinemia

Immune System Disorders: hypersensitivity

Infections and Infestations: bacterial infection, Enterococcal bacteremia, Escherichia bacteremia, Escherichia sepsis, fungal infection, fungal sepsis, gastroenteritis adenovirus, infection, influenza, parainfluenzae virus infection, pneumonia fungal, pneumonia primary atypical, Respiratory syncytial virus infection, sinusitis, staphylococcal infection

Investigations: blood creatinine increased

Psychiatric Disorders: mental status change

Respiratory, Thoracic and Mediastinal Disorder: pulmonary edema

Table 2 lists the incidence of treatment-emergent laboratory abnormalities after clofarabine administration at 52 mg/m^2 among pediatric patients with ALL and AML (N=115).

Table 2: Incidence of Treatment-Emergent Laboratory Abnormalities after Clofarabine Administration

Parameter | Any Grade | Grade 3 or higher
Anemia (N=114) | 83% | 75%
Leukopenia (N=114) | 88% | 88%
Lymphopenia (N=113) | 82% | 82%
Neutropenia (N=113) | 64% | 64%
Thrombocytopenia (N=114) | 81% | 80%
Elevated Creatinine (N=115) | 50% | 8%
Elevated SGOT (N=100) | 74% | 36%
Elevated SGPT (N=113) | 81% | 43%
Elevated Total Bilirubin (N=114) | 45% | 13%

6.2 Postmarketing Experience

The following adverse reactions have been identified during post-approval use of clofarabine injection. Because these reactions are reported voluntarily from a population of uncertain size, it is not always possible to reliably estimate their frequency or establish a causal relationship to drug exposure.

Gastrointestinal disorders: gastrointestinal hemorrhage including fatalities.

Metabolism and nutrition disorders: hyponatremia

Skin and subcutaneous tissue disorders: Stevens-Johnson syndrome (SJS), toxic epidermal necrolysis (TEN) (including fatal cases).

8 USE IN SPECIFIC POPULATIONS

8.1 Pregnancy

Risk Summary

In animal reproduction studies, intravenous administration of clofarabine to pregnant rats and rabbits during organogenesis at doses approximately 0.2 to 1-times the maximum recommended human dose of 52 mg/m^2 based on body surface area (BSA) resulted in embryo-fetal mortality, alterations to growth, and structural abnormalities (see Data). Advise pregnant women of the potential risk to a fetus. There are no available data on clofarabine use in pregnant women to evaluate for a drug-associated risk of major birth defects, miscarriage, or adverse maternal or fetal outcomes. Clofarabine should be used during pregnancy only if the potential benefits to the mother outweigh the potential risks, including those to the fetus.

The estimated background risk of major birth defects and miscarriage for the indicated population is unknown. All pregnancies have a background risk of birth defect, loss, or other adverse outcomes. In the U.S. general population, the estimated background risk of major birth defects and miscarriage in clinically recognized pregnancies is 2% to 4% and 15% to 20%, respectively.

Data

Animal data

Intravenous administration of clofarabine to pregnant rats during organogenesis (gestation days [GD] 7 to 17) at doses of 1, 3 or 9 mg/kg/day (equivalent to 6, 18, 54 mg/m^2/day) resulted in maternal toxicities at the 9 mg/kg dose, as indicated by reduced body weights and food consumption. Developmental toxicity (i.e., reduced fetal body weights and increased postimplantation loss) and increased incidences of external, soft tissue, and skeletal malformations and variations (including retarded ossification) were observed at 9 mg/kg/day (54 mg/m^2; approximately equivalent to the recommended human dose based on BSA). Altered ossification patterns (extra metacarpal or metatarsal ossification) were observed in single fetuses at lower doses of clofarabine (1 and 3 mg/kg/day; 0.1- and 0.3-times the recommended human dose based on BSA).

When clofarabine was administered intravenously to pregnant rabbits during organogenesis (GD 6 to 18) at doses of 0.1, 0.3, or 1 mg/kg/day (equivalent to 1.2, 3.6, 12 mg/m^2/day), developmental toxicity (i.e., reduced fetal body weights and increased postimplantation loss) and increased incidences of external, soft tissue, and skeletal malformations and variations (including retarded ossification) were observed at the 1 mg/kg/day dose (12 mg/m^2; 0.2-times the recommended human dose based on BSA). Alterations in ossification patterns (increase in the average numbers of ossified thoracic vertebrae and rib pairs, and reduction in the average number of forepaw metacarpals) and abdominal wall defect were observed at 0.3 mg/kg/day (3.6 mg/m^2; 0.1-times the recommended human dose based on BSA).

8.2 Lactation

Risk Summary

There are no data on the presence of clofarabine in human milk, the effects on the breastfed child, or the effects on milk production. Because of the potential for serious adverse reactions in the breastfed child including genotoxicity, advise patients not to breastfeed during treatment with clofarabine, and for 2 weeks after the last dose.

8.3 Females and Males of Reproductive Potential

Clofarabine can cause embryo-fetal harm when administered to pregnant women [see Use in Specific Populations (8.1)].

Pregnancy Testing

Pregnancy testing is recommended for females of reproductive potential prior to initiating clofarabine injection.

Contraception

Females

Advise female patients to use effective contraception during treatment with clofarabine injection and for 6 months after the last dose.

Males

Based on genotoxicity findings, advise males with female partners of reproductive potential to use effective contraception during treatment with clofarabine injection and for 3 months after the last dose [see Nonclinical Toxicology (13.1)].

Infertility

Females

Based on findings from animal studies, clofarabine may impair female fertility [see Nonclinical Toxicology (13.1)]. The reversibility of the effect on fertility is unknown.

Males

Based on findings from animal studies, clofarabine may impair male fertility [see Nonclinical Toxicology (13.1)]. The reversibility of the effect on fertility is unknown.

8.4 Pediatric Use

Safety and effectiveness have been established in pediatric patients 1 to 21 years old with relapsed or refractory acute lymphoblastic leukemia.

8.5 Geriatric Use

Safety and effectiveness of clofarabine injection has not been established in geriatric patients aged 65 and older.

8.6 Renal Impairment

Reduce the clofarabine injection starting dose by 50% in patients with CrCL of 30 to 60 mL/min. There is insufficient information to make a dosage recommendation in patients with CrCL less than 30 mL/min or in patients on dialysis.

The pharmacokinetics of clofarabine in patients with renal impairment and normal renal function were obtained from a population pharmacokinetic analysis of three pediatric and two adult studies. In patients with CrCL 60 to less than 90 mL/min (N=47) and CrCL 30 to less than 60 mL/min (N=30), the average AUC of clofarabine increased by 60% and 140%, respectively, compared to patients with normal (N=66) renal function (CrCL greater than 90 mL/min).

10 OVERDOSAGE

There were no known overdoses of clofarabine injection. The highest daily dose administered to a human to date (on a mg/m^2 basis) has been 70 mg/m^2/day × 5 days (2 pediatric ALL patients). The toxicities included in these 2 patients included Grade 4 hyperbilirubinemia, Grade 2 and 3 vomiting, and Grade 3 maculopapular rash.

In a Phase 1 study of adults with refractory and/or relapsed hematologic malignancies, the recommended pediatric dose of 52 mg/m^2/day was not tolerated.

11 DESCRIPTION

Clofarabine injection contains clofarabine, a purine nucleoside metabolic inhibitor. The chemical name of clofarabine is 2-chloro-9-(2-deoxy-2-fluoro-β-D-arabinofuranosyl)-9H-purin-6-amine. Its molecular formula is C10H11ClFN5O3 with a molecular weight of 303.68 Daltons.

The molecular structure of clofarabine is:

Clofarabine injection (1 mg/mL) is supplied in a 20 mL, single-dose vial. The 20 mL vial contains 20 mg clofarabine formulated in 20 mL unbuffered normal saline (comprised of Water for Injection, USP, and Sodium Chloride, USP). The pH range of the solution is 4.5 to 7.5. The solution is sterile, clear and practically colorless, and is preservative-free.

12 CLINICAL PHARMACOLOGY

12.1 Mechanism of Action

Clofarabine is sequentially metabolized intracellularly to the 5’-monophosphate metabolite by deoxycytidine kinase and mono- and di-phospho-kinases to the active 5’-triphosphate metabolite. Clofarabine has affinity for the activating phosphorylating enzyme, deoxycytidine kinase, equal to or greater than that of the natural substrate, deoxycytidine. Clofarabine inhibits DNA synthesis by decreasing cellular deoxynucleotide triphosphate pools through an inhibitory action on ribonucleotide reductase, and by terminating DNA chain elongation and inhibiting repair through incorporation into the DNA chain by competitive inhibition of DNA polymerases. Theaffinity of clofarabine triphosphate for these enzymes is similar to or greater than that of deoxyadenosine triphosphate. In preclinical models, clofarabine has demonstrated the ability to inhibit DNA repair by incorporation into the DNA chain during the repair process. Clofarabine 5’-triphosphate also disrupts the integrity of mitochondrial membrane, leading to the release of the pro-apoptotic mitochondrial proteins, cytochrome C and apoptosis-inducing factor, leading to programmed cell death.

Clofarabine is cytotoxic to rapidly proliferating and quiescent cancer cell types in vitro.

12.3 Pharmacokinetics

The population pharmacokinetics of clofarabine were studied in 40 pediatric patients aged 2 to 19 years (21 males/19 females) with relapsed or refractory acute lymphoblastic leukemia (ALL) or acute myelogenous leukemia (AML). At the given 52 mg/m^2 dose, similar concentrations were obtained over a wide range of body surface areas (BSAs). Clofarabine was 47% bound to plasma proteins, predominantly to albumin. Based on non-compartmental analysis, systemic clearance and volume of distribution at steadystate were 28.8 L/h/m^2 and 172 L/m^2, respectively. The terminal half-life was 5.2 hours. No apparent difference in pharmacokinetics was observed between patients with ALL and AML or between males and females.

No relationship between clofarabine or clofarabine triphosphate exposure and toxicity or response was found in this population.

Based on 24-hour urine collections in the pediatric studies, 49% to 60% of the dose is excreted in the urine unchanged. In vitro studies using isolated human hepatocytes indicate very limited metabolism (0.2%). The pathways of non-hepatic elimination remain unknown.

Clofarabine has not been studied in patients with hepatic impairment

Drug-Drug Interactions

In vitro studies suggested that clofarabine undergoes limited metabolism and does not inhibit or induce major CYP enzymes. CYP inhibitors and inducers are unlikely to affect the metabolism of clofarabine. Clofarabine is unlikely to affect the metabolism of CYP substrates. However, no in vivo drug interaction studies have been conducted.

An in vitro transporter study suggested that clofarabine is a substrate of human transporters OAT1, OAT3, and OCT1. A preclinical study using perfused rat kidney demonstrated that the renal excretion of clofarabine was decreased by cimetidine, an inhibitor of the hOCT2. Although the clinical implications of this finding have not been determined, signs of clofarabine injection toxicity should be monitored when administered with other hOAT1, hOAT3, hOCT1 and hOCT2 substrates or inhibitors.

13 NONCLINICAL TOXICOLOGY

13.1 Carcinogenesis, Mutagenesis, Impairment of Fertility

Clofarabine has not been tested for carcinogenic potential.

Clofarabine was clastogenic in the in vitro mammalian cell chromosome aberration assay (CHO cells) and in the in vivo rat micronucleus assay. Clofarabine was not mutagenic in the bacterial mutation assay (Ames test).

Studies in mice, rats, and dogs have demonstrated dose-related adverse effects on male reproductive organs. Seminiferous tubule and testicular degeneration and atrophy were reported in male mice receiving intraperitoneal doses of 3 mg/kg/day (approximately 0.2-times the recommended human dose based on body surface area [BSA]). Rats receiving 25 mg/kg/day (approximately 3-times the recommended human dose based on BSA) in a 6-month intravenous study had testicular findings of bilateral degeneration of the seminiferous epithelium with retained spermatids and atrophy of interstitial cells. In a 6-month intravenous dog study, cell degeneration of the epididymis and degeneration of the seminiferous epithelium in the testes were observed at 0.375 mg/kg/day (approximately 0.1-times the recommended human dose on a BSA basis). Ovarian atrophy or degeneration and uterine mucosal apoptosis were observed in female mice at 75 mg/kg/day (approximately 4-times the recommended human dose on a mg/m^2 basis), the only dose administered to female mice.

14 CLINICAL STUDIES

Seventy-eight (78) pediatric patients with ALL were exposed to clofarabine. Seventy (70) of the patients received the recommended pediatric dose of clofarabine 52 mg/m^2 daily for 5 days as an intravenous infusion.

Dose Escalation Study in Pediatric Patients with Hematologic Malignancies

The safety and efficacy of clofarabine were evaluated in pediatric patients with refractory or relapsed hematologic malignancies in an open-label, dose-escalation, noncomparative study (NCT00042341, A Phase II, Open Label Study of Clofarabine in Pediatric Patients With Refractory or Relapsed Acute Lymphoblastic Leukemia). The starting dose of clofarabine was 11.25 mg/m^2/day intravenous infusion daily × 5 and escalated to 70 mg/m^2/day intravenous infusion daily × 5. This dosing schedule was repeated every 2 to 6 weeks depending on toxicity and response. Nine of 17 ALL patients were treated with clofarabine 52 mg/m^2 daily for 5 days. In the 17 ALL patients there were 2 complete remissions (12%) and 2 partial remissions (12%) at varying doses. Dose-limiting toxicities in this study were reversible hyperbilirubinemia and elevated transaminase levels and skin rash, experienced at 70 mg/m^2. As a result of this study, the recommended dose for subsequent study in pediatric patients was determined to be 52 mg/m^2/day for 5 days.

Single-Arm Study in Pediatric ALL

Clofarabine was evaluated in an open-label, single-arm study (NCT00042341) of 61 pediatric patients with relapsed/refractory ALL. Patients received a dose of 52 mg/m^2 intravenous infusion over 2 hours for 5 consecutive days repeated every 2 to 6 weeks for up to 12 cycles. There was no dose escalation in this study.

All patients had disease that had relapsed after and/or was refractory to two or more prior therapies. Most patients, 38/61 (62%), had received >2 prior regimens and 18/61 (30%) of the patients had undergone at least 1 prior transplant. The median age of the treated patients was 12 years, 61% were male, 39% were female, 44% were White, 38% were Hispanic or Latino, 12% were Black or African-American, 2% were Asian and 5% were Other race.

The overall remission (OR) rate (Complete Remission [CR] + CR in the absence of total platelet recovery [CRp]) was evaluated. CR was defined as no evidence of circulating blasts or extramedullary disease, an M1 bone marrow (≤5% blasts), and recovery of peripheral counts [platelets ≥100 × 109/L and absolute neutrophil count (ANC) ≥1 × 109/L]. CRp was defined as meeting all criteria for CR except for recovery of platelet counts to ≥100 × 109/L. Partial Response (PR) was also determined, defined as complete disappearance of circulating blasts, an M2 bone marrow (≥5% and ≤25% blasts), and appearance of normal progenitor cells or an M1 marrow that did not qualify for CR or CRp. Duration of remission was also evaluated.

Transplantation rate was not a study endpoint.

Response rates for these studies were determined by an unblinded Independent Response Review Panel (IRRP).

Table 3 summarizes results for the pediatric ALL study. Responses were seen in both pre-B and T-cell immunophenotypes of ALL. The median cumulative dose was 530 mg (range 29 to 2815 mg) in 1 (41%), 2 (44%) or 3 or more (15%) cycles. The median number of cycles was 2 (range 1 to 12). The median time between cycles was 28 days with a range of 12 to 55 days.

Table 3: Results in Single-Arm Pediatric ALL

 | N = 61
CR % [95% CI] | 11.5 (4.7, 22.2)
CRp % [95% CI] | 8.2 (2.7, 18.1)
Median Duration of CR plus CRp (range in weeks)^1 | 10.7 (4.3 to 58.6)

CR = Complete response

CRp = Complete response without platelet recovery

^1Does not include 4 patients who were transplanted (duration of response, including response after transplant, in these 4 patients was 28.6 to 107.7 weeks).

The median duration of CR, including patients who received transplantation, was 47.9 weeks (range 4.3 to 107.7+), where + indicates the patient was still in CR by the study end.

Of 35 patients who were refractory to their immediately preceding induction regimen, 6 (17%) achieved a CR or CRp. Of 18 patients who had at least 1 prior hematopoietic stem cell transplant (HSCT), 5 (28%) achieved a CR or CRp.

Among the 12 patients who achieved at least a CRp, 6 patients achieved the best response after 1 cycle of clofarabine, 5 patients required 2 courses and 1 patient achieved a CR after 3 cycles of therapy.

15 REFERENCES

1. OSHA Hazardous Drugs. OSHA. http://www.osha.gov/SLTC/hazardousdrugs/index.html.

16 HOW SUPPLIED/STORAGE AND HANDLING

Clofarabine injection is supplied in single-dose flint vials containing 20 mg of clofarabine in 20 mL of solution. Each box contains one clofarabine injection vial (NDC 43598-309-20). The 20 mL flint vials contain 20 mL (20 mg) of solution. The pH range of the solution is 4.5 to 7.5. The solution is sterile, clear and practically colorless, is preservative-free, and is free from foreign matter.

Vials containing undiluted clofarabine injection should be stored at 20°-25°C (68°-77°F); [See USP Controlled Room Temperature]. Do not freeze. Retain in carton until contents are used.

Clofarabine is a hazardous drug. Follow applicable special handling and disposal procedures.^1

17 PATIENT COUNSELING INFORMATION

Hematologic Toxicity

Advise patients to return for regular blood counts and to report any symptoms associated with hematologic toxicity (such as weakness, fatigue, pallor, shortness of breath, easy bruising, petechiae, purpura, fever) to their physician [see Warnings and Precautions (5.1)].

Infection

Advise patients of the signs or symptoms of infection (e.g., fever) and report to the physician immediately if any occur [see Warnings and Precautions (5.3)].

Hepatic and Renal Toxicity

Advise patients to avoid medications including over the counter and herbal medications, which may be hepatotoxic or nephrotoxic, during the 5 days of clofarabine injection administration. Also, advise patients of the possibility of developing liver function abnormalities and to immediately report signs or symptoms of jaundice. Advise patients of the signs or symptoms of renal failure/acute renal failure [see Warnings and Precautions (5.7, 5.8)].

Systemic Inflammatory Response Syndrome (SIRS)/Capillary Leak Syndrome

Advise patients of the signs or symptoms of SIRS, such as fever, tachycardia, tachypnea, dyspnea and symptoms suggestive of hypotension [see Warnings and Precautions (5.5)].

Pregnancy

Advise pregnant women and females of reproductive potential of the potential risk to a fetus. Advise females to inform their healthcare provider of a known or suspected pregnancy [see Warnings and Precautions (5.11), Use in Specific Populations (8.3)]. Advise female patients of reproductive potential to use effective contraception during treatment with clofarabine injection and for 6 months after the last dose [see Use in Specific Populations (8.3)]. Advise males with female partners of reproductive potential to use effective contraception during treatment with clofarabine injection and for 3 months after the last dose [see Use in Specific Populations (8.3), Nonclinical Toxicology (13.1)].

Lactation

Advise females not to breastfeed during treatment with clofarabine injection and for 2 weeks after the last dose [see Use in Specific Populations (8.2)].

Gastrointestinal Disorders

Advise patients that they may experience nausea, vomiting, and/or diarrhea with clofarabine injection. If these symptoms are significant, they should seek medical attention [see Warnings and Precautions (5.9)].

Rash

Advise patients that they may experience skin rash with clofarabine injection. If this symptom is significant, they should seek medical attention.

Rx Only

Distributor: Dr. Reddy’s Laboratories Inc.,

Princeton, NJ 08540

Made in India

Issued: 07/2022

PACKAGE LABEL PRINCIPAL DISPLAY PANEL SECTION

Clofarabine Injection 20 mg/20 mL (1 mg/mL)

Vial Label

PACKAGE LABEL

Unvarnished Area Consists of: 2D Barcode, Lot Number, Expiry Date and Serial Number

Clofarabine Injection 20 mg/20 mL (1 mg/mL)

Carton Label